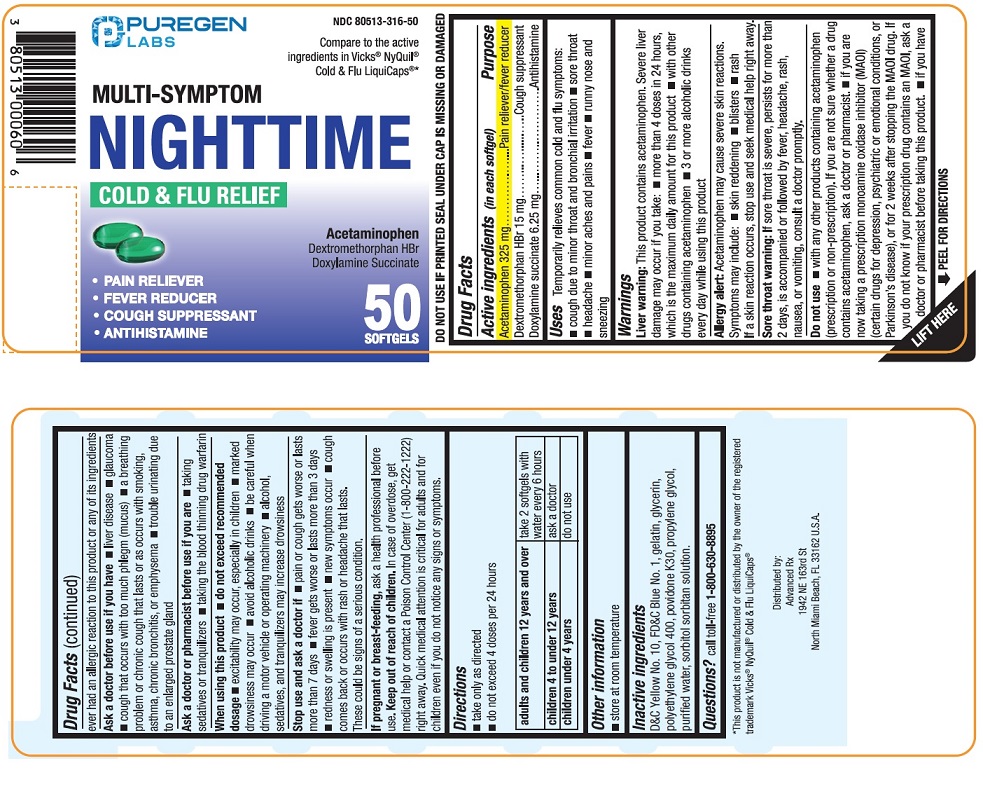 DRUG LABEL: Multi-Symptom Nighttime Cold and Flu Relief
NDC: 80513-316 | Form: CAPSULE, LIQUID FILLED
Manufacturer: Advanced Rx LLC
Category: otc | Type: HUMAN OTC DRUG LABEL
Date: 20250101

ACTIVE INGREDIENTS: ACETAMINOPHEN 325 mg/1 1; DEXTROMETHORPHAN HYDROBROMIDE 15 mg/1 1; DOXYLAMINE SUCCINATE 6.25 mg/1 1
INACTIVE INGREDIENTS: D&C YELLOW NO. 10; FD&C BLUE NO. 1; GELATIN; GLYCERIN; POLYETHYLENE GLYCOL 400; POVIDONE K30; PROPYLENE GLYCOL; WATER; SORBITAN; SORBITOL SOLUTION

Multi-Symptom Night-Time Cold and Flu Relief Softgels

Active ingredients (in each Softgels)

Acetaminophen 325 mg

Dextromethorphan HBr 15 mg

Doxylamine succinate 6.25 mg

Purpose

Pain reliever/Fever reducer
Cough suppressant
Antihistamine

Uses

Temporarily relieves common cold and flu symptoms:

- cough due to minor throat and bronchial irritation
- sore throat
- headache
- minor aches and pains
- fever
- runny nose and sneezing

Warnings

Liver warning:This product contains acetaminophen. Severe liver damage may occur if you take:

- more than 4 doses in 24 hours, which is the maximum daily amount for this product
- with other drugs containing acetaminophen
- 3 or more alcoholic drinks every day while using this product

Allergy alert:Acetaminophen may cause severe skin reactions. Symptoms may include:

- skin reddening
- blisters
- rash

If a skin reaction occurs, stop use and seek medical help right away.

Sore throat warning:If sore throat is severe, persists for more than 2 days, is accompanied or followed by fever, headache, rash,
nausea, or vomiting, consult a doctor promptly

Do not use

- with any other drug containing acetaminophen (prescription or non-prescription).
- if you are not sure whether a drug contains acetaminophen, ask a doctor or pharmacist.
- if you are now taking a prescription monoamine oxidase inhibitor (MAOI) (certain drugs for depression, psychiatric or emotional conditions, or Parkinson’s disease), or for 2 weeks after stopping the MAOI drug. If you do not know if your prescription drug contains an MAOI, ask a doctor or pharmacist before taking this product.
- if you have ever had an allergic reaction to this product or any of its ingredients

Ask a doctor before use if you have

- liver disease
- glaucoma
- cough that occurs with too much phlegm (mucus)
- a breathing problem or chronic cough that lasts or as occurs with smoking, asthma, chronic bronchitis or emphysema
- trouble urinating due to enlarged prostate gland

Ask a doctor or pharmacist before use if you are

- taking sedatives or tranquilizers
- taking the blood thinning drug warfarin

When using this product

- do not exceed recommended dosage
- excitability may occur, especially in children
- marked drowsiness may occur
- avoid alcoholic drinks
- be careful when driving a motor vehicle or operating machinery
- alcohol, sedatives, and tranquilizers may increase drowsiness

Stop use and ask a doctor if

- pain or cough gets worse or lasts more than 7 days
- fever gets worse or lasts more than 3 days
- redness or swelling is present
- new symptoms occur
- cough comes back or occurs with rash or headache that lasts.

These could be signs of a serious condition.

PREGNANCY OR BREAST FEEDING

If pregnant or breast-feeding,ask a health professional before use.

Keep out of reach of children

In case of overdose, get medical help or contact a Poison Control Center (1-800-222-1222) right away. Quick medical attention is critical for adults and for children even if you do not notice any signs or symptoms.

Direction

- take only as directed
- do not exceed 4 doses per 24 hours

adults and children 12 years and over | take 2 softgels with water every 6 hours
children 4 to under 12 years | ask a doctor
children under 4 years | do not use

Other information

- store at room temperature.
- DO NOT USE IF PRINTED SEAL UNDER CAP IS MISSING OR DAMAGED.

Inactive ingredients

D&C Yellow No10, FD&C Blue No 1, gelatin, glycerin, polyethylene glycol 400, povidone K30, propylene glycol, purified water, sorbitol sorbitan solution.

Questions?

call toll-free 1-800-630-8895

Distributed by:

Advanced Rx

1942 NE 163rd St,

North Miami Beach, FL 33162 U.S.A.

PACKAGE LABEL

NDC 80513-316-50

*Compare to the active ingredients in Vicks®NyQuil®Cold & Flu LiquiCaps®

50 Softgels

MULTI-SYMPTOM NIGHTTIME COLD & FLU RELIFE

Acetaminophen,

Dextromethorphan HBr,

Doxylamine Succinate

• Pain Reliever

• Fever Reducer

• Cough Suppressant

• Antihistamine

*This product is not manufactured or distributed by the owner of the registered trademark Vicks®NyQuil®Cold & Flu LiquiCaps®